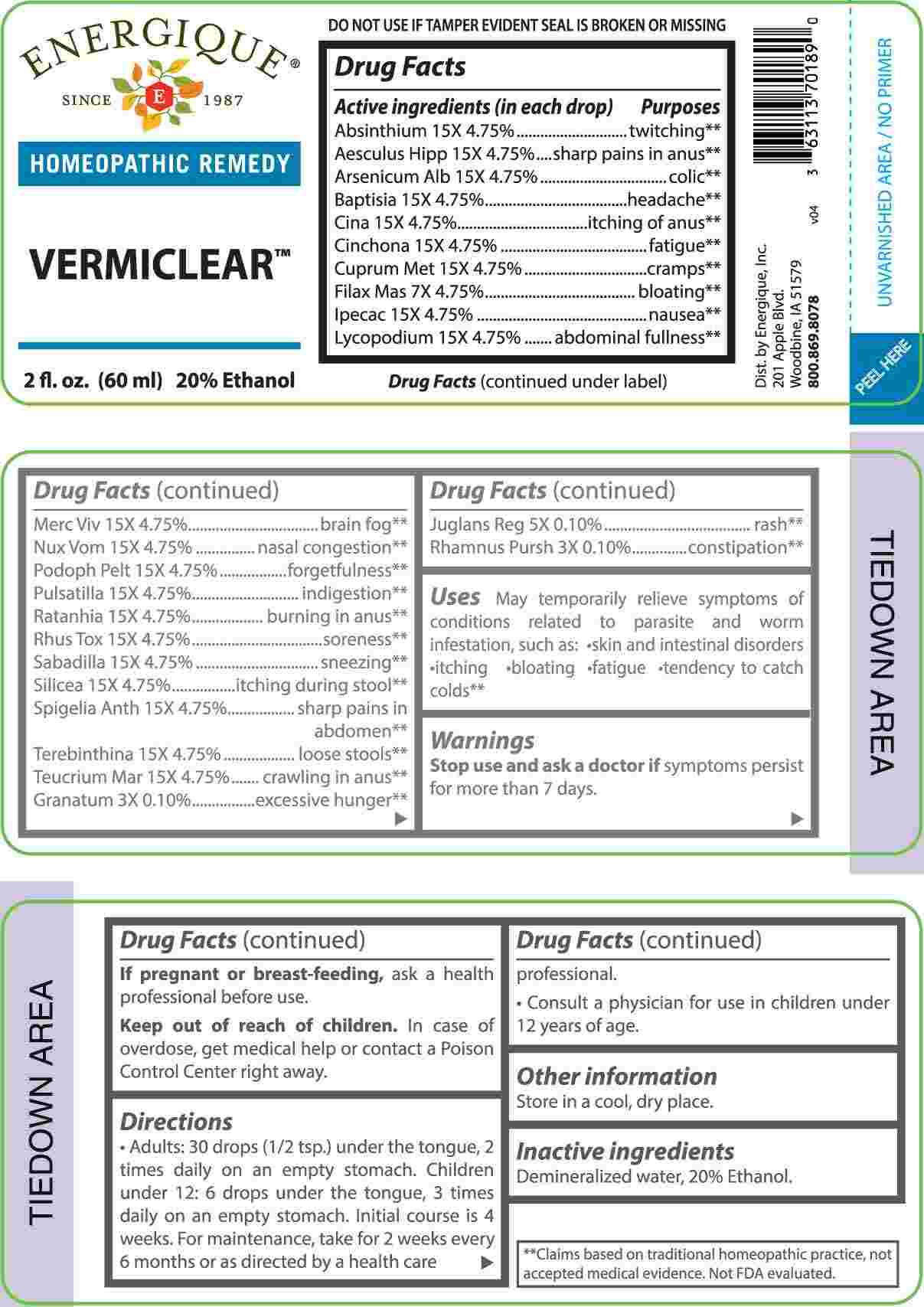 DRUG LABEL: Vermiclear
NDC: 44911-0718 | Form: LIQUID
Manufacturer: Energique, Inc.
Category: homeopathic | Type: HUMAN OTC DRUG LABEL
Date: 20240805

ACTIVE INGREDIENTS: PUNICA GRANATUM ROOT BARK 3 [hp_X]/1 mL; FRANGULA PURSHIANA BARK 3 [hp_X]/1 mL; JUGLANS REGIA LEAF 5 [hp_X]/1 mL; JUGLANS REGIA FRUIT RIND, IMMATURE 5 [hp_X]/1 mL; DRYOPTERIS FILIX-MAS ROOT 7 [hp_X]/1 mL; WORMWOOD 15 [hp_X]/1 mL; HORSE CHESTNUT 15 [hp_X]/1 mL; ARSENIC TRIOXIDE 15 [hp_X]/1 mL; BAPTISIA TINCTORIA ROOT 15 [hp_X]/1 mL; ARTEMISIA CINA PRE-FLOWERING TOP 15 [hp_X]/1 mL; CINCHONA OFFICINALIS BARK 15 [hp_X]/1 mL; COPPER 15 [hp_X]/1 mL; IPECAC 15 [hp_X]/1 mL; LYCOPODIUM CLAVATUM SPORE 15 [hp_X]/1 mL; MERCURY 15 [hp_X]/1 mL; STRYCHNOS NUX-VOMICA SEED 15 [hp_X]/1 mL; PODOPHYLLUM 15 [hp_X]/1 mL; PULSATILLA VULGARIS WHOLE 15 [hp_X]/1 mL; KRAMERIA LAPPACEA ROOT 15 [hp_X]/1 mL; TOXICODENDRON PUBESCENS LEAF 15 [hp_X]/1 mL; SCHOENOCAULON OFFICINALE SEED 15 [hp_X]/1 mL; SILICON DIOXIDE 15 [hp_X]/1 mL; SPIGELIA ANTHELMIA WHOLE 15 [hp_X]/1 mL; TURPENTINE OIL 15 [hp_X]/1 mL; TEUCRIUM MARUM WHOLE 15 [hp_X]/1 mL
INACTIVE INGREDIENTS: WATER; ALCOHOL

DRUG FACTS:

ACTIVE INGREDIENTS:

(in each drop) Absinthium 15X 4.75%, Aesculus Hippocastanum 15X 4.75%, Arsenicum Album 15X 4.75%, Baptisia Tinctoria 15X 4.75%, Cina 15X 4.75%, Cinchona Officinalis 15X 4.75%, Cuprum Metallicum 15X 4.75%, Filix Mas 7X 4.75%, Ipecacuanha 15X 4.75%, Lycopodium Clavatum 15X 4.75%, Mercurius Vivus 15X 4.75%, Nux Vomica 15X 4.75%, Podophyllum Peltatum 15X 4.75%, Pulsatilla 15X 4.75%, Ratanhia 15X 4.75%, Rhus Tox 15X 4.75%, Sabadilla 15X 4.75%, Silicea 15X 4.75%, Spigelia Anthelmia 15X 4.75%, Terebinthina 15X 4.75%, Teucrium Marum 15X 4.75%, Granatum 3X 0.10%, Juglans Regia 5X 0.10, Rhamnus Purshiana 3X 0.10%.

PURPOSE:

Absinthium - twitching,** Aesculus Hippocastanum – sharp pains in anus,** Arsenicum Album - colic,** Baptisia Tinctoria - headache,** Cina – itching of anus,** Cinchona Officinalis - fatigue,** Cuprum Metallicum - cramps,** Filix Mas - bloating,** Ipecacuanha - nausea,** Lycopodium Clavatum – abdominal fullness,** Mercurius Vivus – brain fog,** Nux Vomica – nasal congestion,** Podophyllum Peltatum - forgetfulness,** Pulsatilla - indigestion,** Ratanhia – burning in anus,** Rhus Tox - soreness,** Sabadilla - sneezing,** Silicea – itching during stool,** Spigelia Anthelmia – sharp pains in abdomen,** Terebinthina – loose stools,** Teucrium Marum – crawling in anus,** Granatum – excessive hunger,** Juglans Regia - rash,** Rhamnus Purshiana – constipation**

**Claims based on traditional homeopathic practice, not accepted medical evidence. Not FDA evaluated.

USES:

May temporarily relieve symptoms of conditions related to parasite and worm infestation, such as:

• skin and intestinal disorders • itching • bloating • fatigue • tendency to catch colds.**

**Claims based on traditional homeopathic practice, not accepted medical evidence. Not FDA evaluated.

WARNINGS:

Stop use and ask a doctor if symptoms persist for more than 7 days.

If pregnant or breast-feeding, ask a health professional before use.

Keep out of reach of children. In case of overdose get medical help or contact a Poison Control Center right away.

DO NOT USE IF TAMPER EVIDENT SEAL IS BROKEN OR MISSING

Store in a cool, dry place.

KEEP OUT OF REACH OF CHILDREN:

In case of overdose get medical help or contact a Poison Control Center right away.

DIRECTIONS:

• Adults: 30 drops (1/2 tsp.) under the tongue, 2 times daily on an empty stomach. Children under 12: 6 drops under the tongue, 3 times daily on an empty stomach. Initial course is 4 weeks. For maintenance, take for 2 weeks every 6 months or as directed by a health care professional. • Consult a physician for use in children under 12 years of age.

INACTIVE INGREDIENTS:

Demineralized water, 20% Ethanol.

QUESTIONS:

Dist. by Energique, Inc.

201 Apple Blvd.

Woodbine, IA 51579

800.869.8078

PACKAGE LABEL DISPLAY:

ENERGIQUE

SINCE 1987

HOMEOPATHIC REMEDY

VERMICLEAR

2 fl. oz. (60 ml)